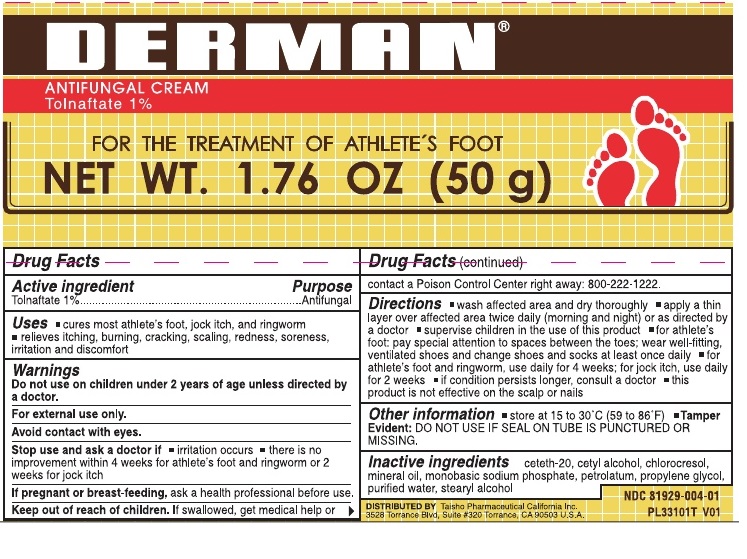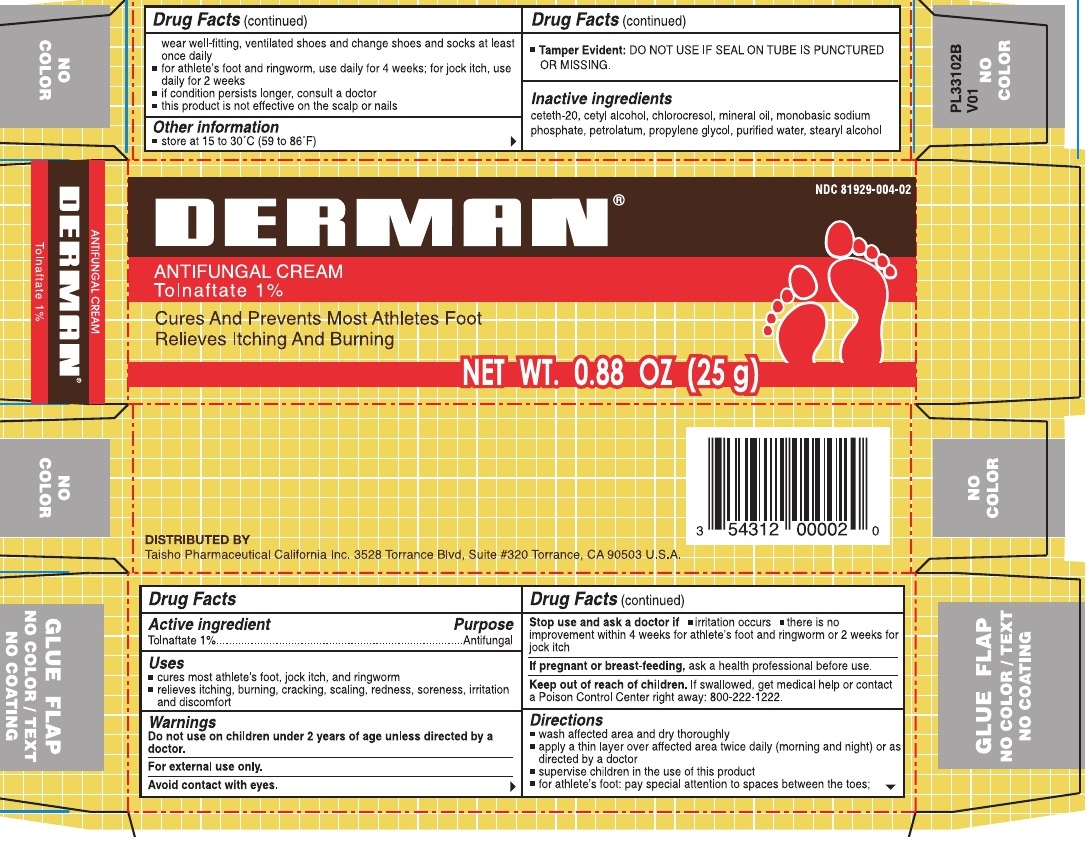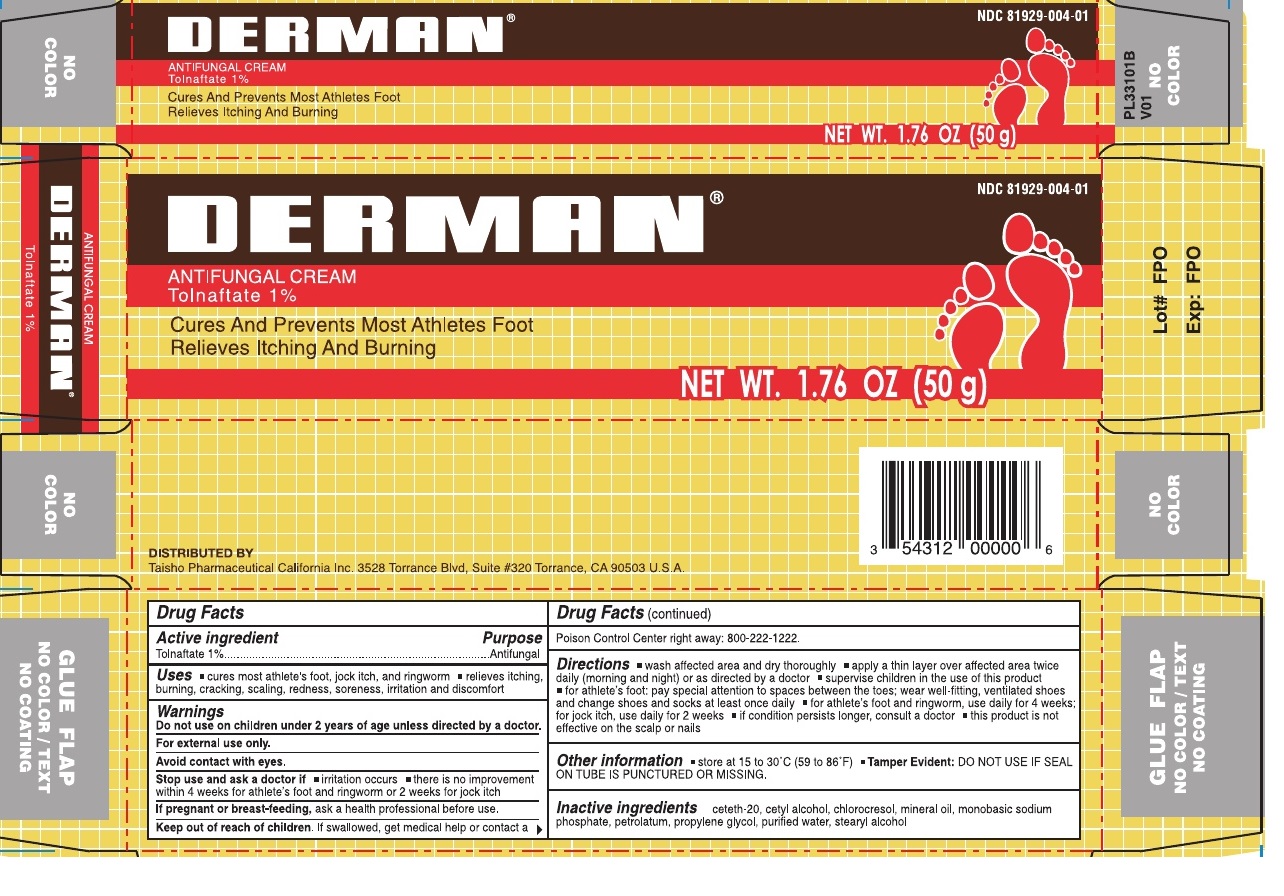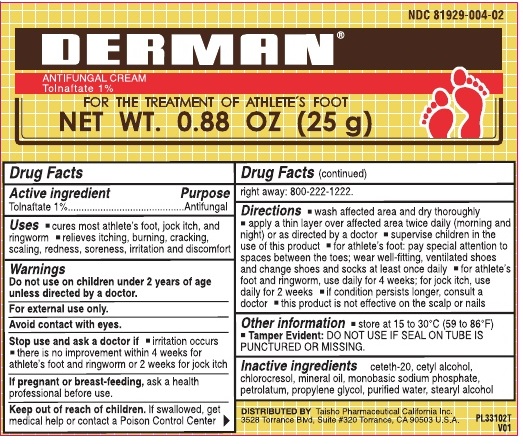 DRUG LABEL: Derman antifungal cream
NDC: 81929-004 | Form: CREAM
Manufacturer: Taisho Pharmaceutical California Inc.
Category: otc | Type: HUMAN OTC DRUG LABEL
Date: 20250807

ACTIVE INGREDIENTS: TOLNAFTATE 10 mg/1 g
INACTIVE INGREDIENTS: CETETH-20; CETYL ALCOHOL; CHLOROCRESOL; MINERAL OIL; SODIUM PHOSPHATE, MONOBASIC, UNSPECIFIED FORM; PETROLATUM; PROPYLENE GLYCOL; WATER; STEARYL ALCOHOL

Derman antifungal cream

Active ingredient

Tolnaftate 1%

Purpose

Antifungal

Uses

- cures most athlete's foot, jock itch, and ringworm
- relieves itching, burning, cracking, scaling, redness, soreness, irritation and discomfort

Warnings

Do not use

on children under 2 years of age unless directed by a doctor.

For external use only.

Avoid contact with eyes.

Stop use and ask a doctor if

- irritation occurs
- there is no improvement within 4 weeks for athlete's foot and ringworm or 2 weeks for jock itch

If pregnant or breast-feeding,

ask a health professional before use.

Keep out of reach of children.

If swallowed, get medical help or contact a Poison Control Center right away: 800-222-1222.

Directions

- wash affected area and dry thoroughly
- apply a thin layer over affected area twice daily (morning and night) or as directed by a doctor
- supervise children in the use of this product
- for athlete's foot: pay special attention to spaces between the toes; wear well-fitting, ventilated shoes and change shoes and socks at least once daily
- for athlete's foot and ringworm, use daily for 4 weeks; for jock itch, use daily for 2 weeks
- if condition persists longer, consult a doctor
- this product is not effective on the scalp or nails

Other information

store at 15 to 30°C (59° to 86°F)

DO NOT USE IF SEAL ON TUBE IS PUNCTURED OR MISSING. Tamper Evident:

Inactive ingredients

ceteth-20, cetyl alcohol, chlorocresol, mineral oil, monobasic sodium phosphate, petrolatum, propylene glycol, purified water, stearyl alcohol